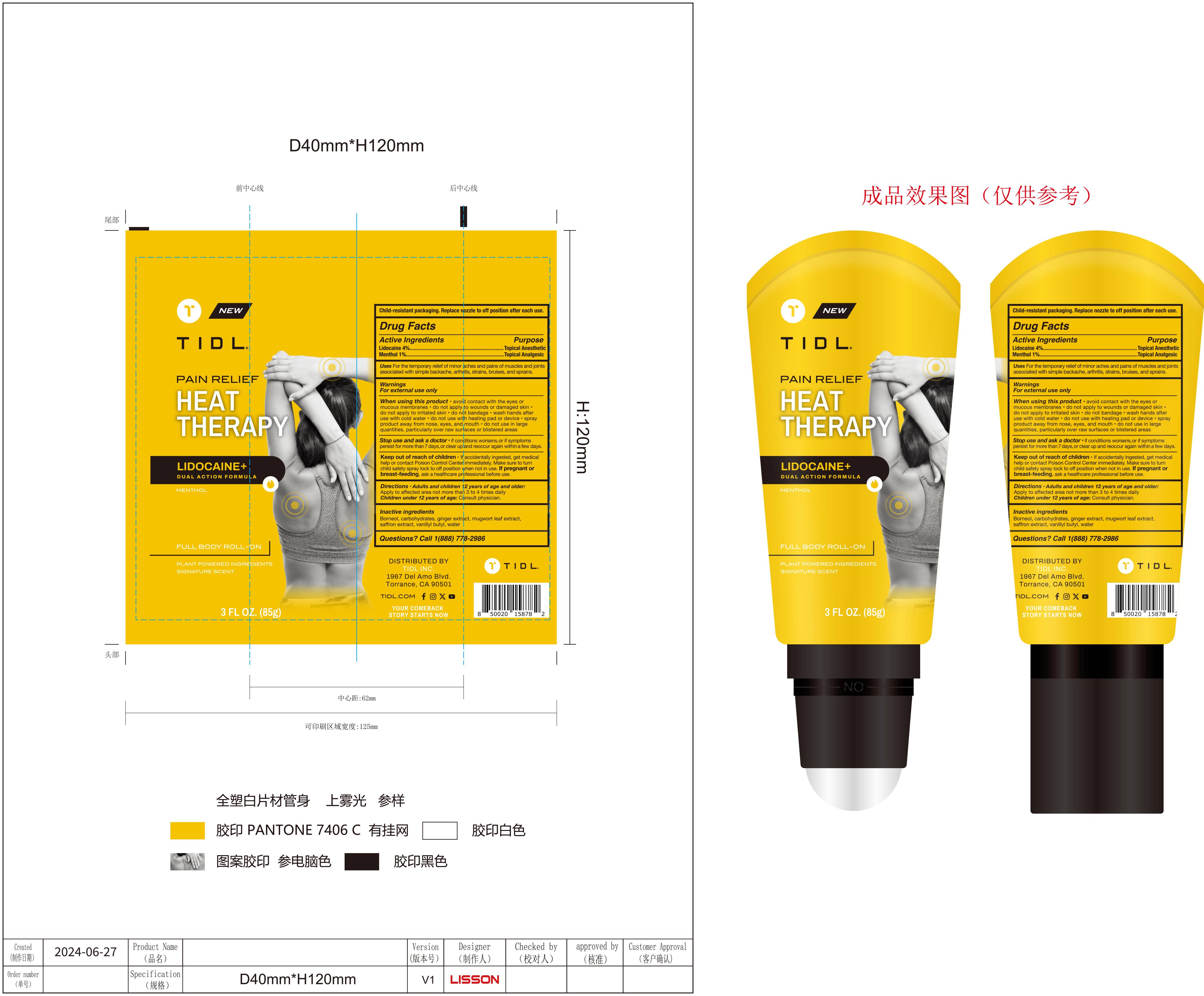 DRUG LABEL: TIDL PAIN RELIEF HEAT THERAPY ROLL-ON
NDC: 84214-002 | Form: GEL
Manufacturer: Shenzhen Sam Technology Co., Ltd.
Category: otc | Type: HUMAN OTC DRUG LABEL
Date: 20240712

ACTIVE INGREDIENTS: MENTHOL 1 g/100 g; LIDOCAINE 4 g/100 g
INACTIVE INGREDIENTS: ARTEMISIA ARGYI LEAF; BORNEOL; CROCUS SATIVUS FLOWER; VANILLYL BUTYL ETHER; WATER; GALECTIN-3; GINGER

84214-002

Active Ingredient

Lidocaine 4%
Menthol 1%

Purpose

Topical Anesthetic
Topical Analgesic

Use

For the temporary relief of minor aches and pains of muscles and joints associated with simple backache, arthritis, strains, bruises, and sprains

Warnings

For external use only

do not use wiih heating pad or device

When Using

·avoid contact with the eyes or mucous membranes
·do not apply to wounds or damaged skin
·do not apply to irritated skin
·do not bandage
·wash hands after use with cool water
·do not use with heating pad or device
·spray product away from nose,eyes,and mouth
·do not use in large quantities, particularly over raw surfaces or blistered areas

Stop Use

if condition worsens, or if symptoms persist for more than 7 days, or clear up and reoccur again within a few days

Ask Doctor

if condition worsens, or if symptoms persist for more than 7 days, or clear up and reoccur again within a few days

Keep Oot Of Reach Of Children

If accidentally ingested, get medical help or contact a Poison Control Center immediately. Make sure to turn child safety spray lock to off position when not in use. If pregnant or breast-feeding, ask a healthcare professional before use.

Directions

·Adults and children 12 years of age and older：Apply to affected area not more than 3 to 4 times daily
·Children under 12 years of age：Consult physician

Inactive ingredients

Borneol, Carbohydrates, Ginger Extract, Mugwort Leaf Extract, Saffron Extract, Vanillyl butyl, Water